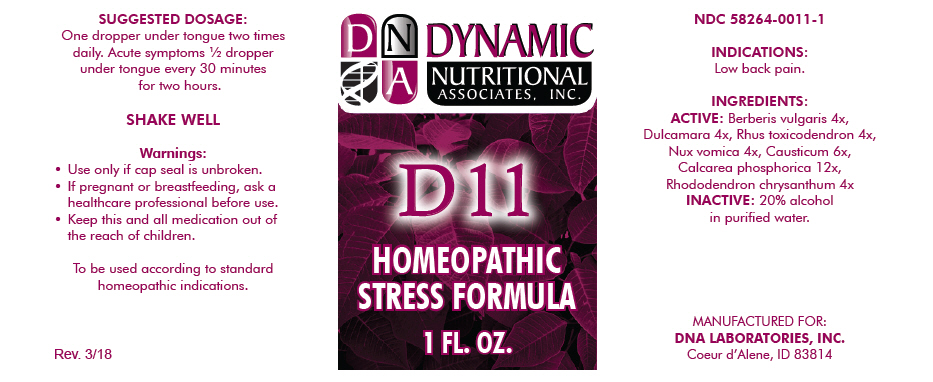 DRUG LABEL: D-11
NDC: 58264-0011 | Form: SOLUTION
Manufacturer: DNA Labs, Inc.
Category: homeopathic | Type: HUMAN OTC DRUG LABEL
Date: 20250113

ACTIVE INGREDIENTS: BERBERIS VULGARIS ROOT BARK 4 [hp_X]/1 mL; SOLANUM DULCAMARA WHOLE 4 [hp_X]/1 mL; TOXICODENDRON PUBESCENS LEAF 4 [hp_X]/1 mL; STRYCHNOS NUX-VOMICA SEED 4 [hp_X]/1 mL; CAUSTICUM 6 [hp_X]/1 mL; TRIBASIC CALCIUM PHOSPHATE 12 [hp_X]/1 mL; RHODODENDRON AUREUM LEAF 4 [hp_X]/1 mL
INACTIVE INGREDIENTS: ALCOHOL; WATER

D-11

NDC 58264-0011-1

INDICATIONS

PURPOSE

Low back pain.

INGREDIENTS

ACTIVE

Berberis vulgaris 4x, Dulcamara 4x, Rhus toxicodendron 4x, Nux vomica 4x, Causticum 6x, Calcarea phosphorica 12x, Rhododendron chrysanthum 4x

INACTIVE

20% alcohol in purified water.

SUGGESTED DOSAGE

One dropper under tongue two times daily. Acute symptoms ½ dropper under tongue every 30 minutes for two hours.

STORAGE AND HANDLING

SHAKE WELL

Warnings

- Use only if cap seal is unbroken.

PREGNANCY OR BREAST FEEDING

- If pregnant or breastfeeding, ask a healthcare professional before use.

KEEP OUT OF REACH OF CHILDREN

- Keep this and all medication out of the reach of children.

To be used according to standard homeopathic indications.

PRINCIPAL DISPLAY PANEL - 1 FL. OZ. Bottle Label

DYNAMIC
NUTRITIONAL
ASSOCIATES, INC.

D 11

HOMEOPATHIC
STRESS FORMULA

1 FL. OZ.